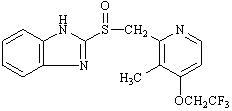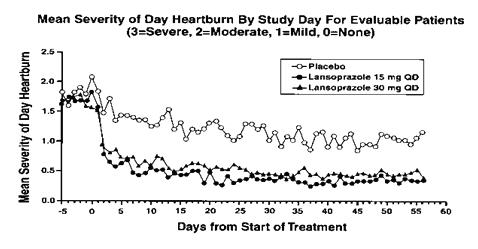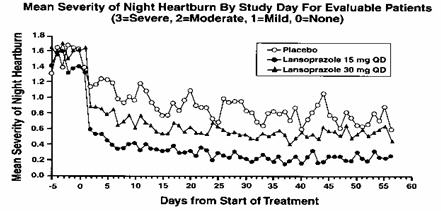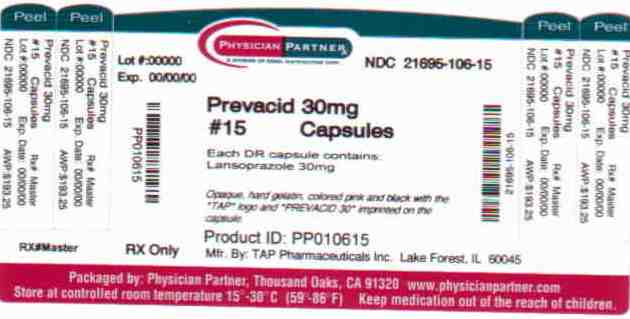 DRUG LABEL: Prevacid SoluTab
NDC: 21695-106 | Form: TABLET, ORALLY DISINTEGRATING, DELAYED RELEASE
Manufacturer: Rebel Distributors Corp
Category: prescription | Type: HUMAN PRESCRIPTION DRUG LABEL
Date: 20110104

ACTIVE INGREDIENTS: lansoprazole 30 mg/1 1

HIGHLIGHTS OF PRESCRIBING INFORMATION

These highlights do not include all the information needed to use PREVACID safely and effectively. See full prescribing information for:
PREVACID (lansoprazole) Delayed-Release Capsules
PREVACID SoluTab (lansoprazole) Delayed-Release Orally Disintegrating Tablets
For oral administration
Initial U.S. Approval: 1995

RECENT MAJOR CHANGES

Dosage and Administration:
Important Administration Information (2.3) | June 2009
Warnings and Precautions:
Bone Fracture (5.2) | August 2010

1 INDICATIONS AND USAGE

PREVACID is a proton pump inhibitor (PPI). Refer to DOSAGE and ADMINISTRATION table (below) for indications and usage.

2 DOSAGE AND ADMINISTRATION

Indication |  | Dose | Frequency
Duodenal Ulcers (1.1, 1.3)
Short-Term Treatment |  | 15 mg | Once daily for 4 wks
Maintenance of Healed |  | 15 mg | Once daily
H. pylori Eradication to Reduce Recurrence of Duodenal Ulcer (1.2)
Triple Therapy: | PREVACID Amoxicillin Clarithromycin | 30 mg 1 gram 500 mg | Twice daily for 10 or 14 days
Dual Therapy: | PREVACID Amoxicillin | 30 mg 1 gram | Three times daily for 14 days
Benign Gastric Ulcer (1.4)
Short-Term Treatment |  | 30 mg | Once daily up to 8 wks
NSAID-associated Gastric Ulcer (1.6)
Healing Risk Reduction |  | 30 mg 15 mg | Once daily for 8 wks Once daily up to 12 wks
GERD (1.7)
Short-Term Treatment of Symptomatic GERD |  | 15 mg | Once daily up to 8 wks
Short-Term Treatment of EE |  | 30 mg | Once daily up to 8 wks
Pediatric (8.4)
(1 to 11 years of age) Short-Term Treatment of Symptomatic GERD and Short-Term Treatment of EE
≤ 30 kg |  | 15 mg | Once daily up to 12 wks
> 30 kg |  | 30 mg | Once daily up to 12 wks
(12 to 17 years of age) Short-Term Treatment of Symptomatic GERD
Nonerosive GERD |  | 15 mg | Once daily up to 8 wks
EE |  | 30 mg | Once daily up to 8 wks
Maintenance of Healing of EE (1.8) |  | 15 mg | Once daily
Pathological Hypersecretory Conditions (i.e., ZES) (1.9) |  | 60 mg | Once daily

3 DOSAGE FORMS AND STRENGTHS

Capsules and Tablets: 15 mg and 30 mg. (3)

4 CONTRAINDICATIONS

Contraindicated in patients with known severe hypersensitivity to any component of the PREVACID formulation. (4)

5 WARNINGS AND PRECAUTIONS

- Symptomatic response with PREVACID does not preclude the presence of gastric malignancy. (5.1)
- Bone Fracture: Long-term and multiple daily dose PPI therapy may be associated with an increased risk for osteoporosis-related fractures of the hip, wrist or spine. (5.2)

6 ADVERSE REACTIONS

Most commonly reported adverse reactions (≥1%): diarrhea, abdominal pain, nausea and constipation. (6)

To report SUSPECTED ADVERSE REACTIONS, contact Takeda Pharmaceuticals America Inc. at 1-877-TAKEDA-7 (1-877-825-3327) or FDA at 1-800-FDA-1088 or www.fda.gov/medwatch.

7 DRUG INTERACTIONS

- Do not co-administer with atazanavir. (7)
- May interfere with the absorption of drugs where gastric pH is important for bioavailability. (7)
- Concomitant warfarin use may require monitoring for increases in INR and prothrombin time. (7)
- Concomitant tacrolimus use may increase tacrolimus whole blood concentrations. (7)
- Titration of theophylline dosage may be required when concomitant PREVACID use is started or stopped. (7)

8 USE IN SPECIFIC POPULATIONS

- Consider dose adjustment in patients with severe liver impairment. (8.7)
- PREVACID is not effective in patients with symptomatic GERD 1 month to less than 1 year of age. (8.4)

FULL PRESCRIBING INFORMATION

1 INDICATIONS AND USAGE

1.1 Short-Term Treatment of Active Duodenal Ulcer

PREVACID is indicated for short-term treatment (for 4 weeks) for healing and symptom relief of active duodenal ulcer [see Clinical Studies (14)].

1.2 H. pylori Eradication to Reduce the Risk of Duodenal Ulcer Recurrence

Triple Therapy: PREVACID/amoxicillin/clarithromycin

PREVACID in combination with amoxicillin plus clarithromycin as triple therapy is indicated for the treatment of patients with H. pylori infection and duodenal ulcer disease (active or one-year history of a duodenal ulcer) to eradicate H. pylori. Eradication of H. pylori has been shown to reduce the risk of duodenal ulcer recurrence [see Clinical Studies (14)].

Please refer to the full prescribing information for amoxicillin and clarithromycin.

Dual Therapy: PREVACID/amoxicillin

PREVACID in combination with amoxicillin as dual therapy is indicated for the treatment of patients with H. pylori infection and duodenal ulcer disease (active or one-year history of a duodenal ulcer) who are either allergic or intolerant to clarithromycin or in whom resistance to clarithromycin is known or suspected (see the clarithromycin package insert, MICROBIOLOGY section). Eradication of H. pylori has been shown to reduce the risk of duodenal ulcer recurrence [see Clinical Studies (14)].

Please refer to the full prescribing information for amoxicillin.

1.3 Maintenance of Healed Duodenal Ulcers

PREVACID is indicated to maintain healing of duodenal ulcers. Controlled studies do not extend beyond 12 months [see Clinical Studies (14)].

1.4 Short-Term Treatment of Active Benign Gastric Ulcer

PREVACID is indicated for short-term treatment (up to 8 weeks) for healing and symptom relief of active benign gastric ulcer [see Clinical Studies (14)].

1.5 Healing of NSAID-Associated Gastric Ulcer

PREVACID is indicated for the treatment of NSAID-associated gastric ulcer in patients who continue NSAID use. Controlled studies did not extend beyond 8 weeks [see Clinical Studies (14)].

1.6 Risk Reduction of NSAID-Associated Gastric Ulcer

PREVACID is indicated for reducing the risk of NSAID-associated gastric ulcers in patients with a history of a documented gastric ulcer who require the use of an NSAID. Controlled studies did not extend beyond 12 weeks [see Clinical Studies (14)].

1.7 Gastroesophageal Reflux Disease (GERD)

Short-Term Treatment of Symptomatic GERD

PREVACID is indicated for the treatment of heartburn and other symptoms associated with GERD [see Clinical Studies (14)].

Short-Term Treatment of Erosive Esophagitis

PREVACID is indicated for short-term treatment (up to 8 weeks) for healing and symptom relief of all grades of erosive esophagitis. For patients who do not heal with PREVACID for 8 weeks (5 to 10%), it may be helpful to give an additional 8 weeks of treatment. If there is a recurrence of erosive esophagitis an additional 8-week course of PREVACID may be considered [see Clinical Studies (14)].

1.8 Maintenance of Healing of Erosive Esophagitis (EE)

PREVACID is indicated to maintain healing of erosive esophagitis. Controlled studies did not extend beyond 12 months [see Clinical Studies (14)].

1.9 Pathological Hypersecretory Conditions Including Zollinger-Ellison Syndrome (ZES)

PREVACID is indicated for the long-term treatment of pathological hypersecretory conditions, including Zollinger-Ellison syndrome [see Clinical Studies (14)].

2 DOSAGE AND ADMINISTRATION

PREVACID is available as a capsule and an orally disintegrating tablet, and is available in 15 mg and 30 mg strengths. Directions for use specific to the route and available methods of administration for each of these dosage forms is presented below. PREVACID should be taken before eating. PREVACID products SHOULD NOT BE CRUSHED OR CHEWED. In the clinical trials, antacids were used concomitantly with PREVACID.

2.1 Recommended Dose

Indication | Recommended Dose | Frequency
Duodenal Ulcers
Short-Term Treatment | 15 mg | Once daily for 4 weeks
Maintenance of Healed | 15 mg | Once daily
H. pylori Eradication to Reduce the Risk of Duodenal Ulcer Recurrence [Please refer to amoxicillin and clarithromycin full prescribing information for CONTRAINDICATIONS and WARNINGS, and for information regarding dosing in elderly and renally-impaired patients.]
Triple Therapy:
PREVACID | 30 mg | Twice daily (q12h) for 10 or 14 days
Amoxicillin | 1 gram | Twice daily (q12h) for 10 or 14 days
Clarithromycin | 500 mg | Twice daily (q12h) for 10 or 14 days
Dual Therapy:
PREVACID | 30 mg | Three times daily (q8h) for 14 days
Amoxicillin | 1 gram | Three times daily (q8h) for 14 days
Benign Gastric Ulcer
Short-Term Treatment | 30 mg | Once daily for up to 8 weeks
NSAID-associated Gastric Ulcer
Healing | 30 mg | Once daily for 8 weeks [Controlled studies did not extend beyond indicated duration.]
Risk Reduction | 15 mg | Once daily for up to 12 weeks
Gastroesophageal Reflux Disease (GERD)
Short-Term Treatment of Symptomatic GERD | 15 mg | Once daily for up to 8 weeks
Short-Term Treatment of Erosive Esophagitis | 30 mg | Once daily for up to 8 weeks [For patients who do not heal with PREVACID for 8 weeks (5 to 10%), it may be helpful to give an additional 8 weeks of treatment. If there is a recurrence of erosive esophagitis, an additional 8 week course of PREVACID may be considered.]
Pediatric
(1 to 11 years of age)
Short-Term Treatment of Symptomatic GERD and Short-Term Treatment of Erosive Esophagitis
≤ 30 kg | 15 mg | Once daily for up to 12 weeks [The PREVACID dose was increased (up to 30 mg twice daily) in some pediatric patients after 2 or more weeks of treatment if they remained symptomatic. For pediatric patients unable to swallow an intact capsule please see Administration Options.]
> 30 kg | 30 mg | Once daily for up to 12 weeks
(12 to 17 years of age)
Short-Term Treatment of Symptomatic GERD
Nonerosive GERD | 15 mg | Once daily for up to 8 weeks
Erosive Esophagitis | 30 mg | Once daily for up to 8 weeks
Maintenance of Healing of Erosive Esophagitis | 15 mg | Once daily
Pathological Hypersecretory Conditions Including Zollinger-Ellison Syndrome | 60 mg | Once daily [Varies with individual patient. Recommended adult starting dose is 60 mg once daily. Doses should be adjusted to individual patient needs and should continue for as long as clinically indicated. Dosages up to 90 mg twice daily have been administered. Daily dose of greater than 120 mg should be administered in divided doses. Some patients with Zollinger-Ellison Syndrome have been treated continuously with PREVACID for more than 4 years.]

2.2 Special Populations

Renal impairment patients and geriatric patients do not require dosage adjustment. However, consider dose adjustment in patients with severe liver impairment [see Use in Specific Populations (8.5, 8.6 and 8.7)].

2.3 Important Administration Information

Administration Options

PREVACID Delayed-Release Capsules – Oral Administration

- PREVACID Delayed-Release Capsules should be swallowed whole.
- Alternatively, for patients who have difficulty swallowing capsules, PREVACID Delayed-Release Capsules can be opened and administered as follows:
  - Open capsule.
  - Sprinkle intact granules on one tablespoon of either applesauce, ENSURE pudding, cottage cheese, yogurt or strained pears.
  - Swallow immediately.
- PREVACID Delayed-Release Capsules may also be emptied into a small volume of either apple juice, orange juice or tomato juice and administered as follows:
  - Open capsule.
  - Sprinkle intact granules into a small volume of either apple juice, orange juice or tomato juice (60 mL – approximately 2 ounces).
  - Mix briefly.
  - Swallow immediately.
  - To ensure complete delivery of the dose, the glass should be rinsed with two or more volumes of juice and the contents swallowed immediately.

PREVACID Delayed-Release Capsules – Nasogastric Tube (≥16 French) Administration

- For patients who have a nasogastric tube in place, PREVACID Delayed-Release Capsules can be administered as follows:
  - Open capsule.
  - Mix intact granules into 40 mL of apple juice. DO NOT USE OTHER LIQUIDS.
  - Inject through the nasogastric tube into the stomach.
  - Flush with additional apple juice to clear the tube.

USE IN OTHER FOODS AND LIQUIDS HAS NOT BEEN STUDIED CLINICALLY AND IS THEREFORE NOT RECOMMENDED.

PREVACID SoluTab Delayed-Release Orally Disintegrating Tablets

- PREVACID SoluTab should not be broken or cut.
- PREVACID SoluTab should not be chewed.
  - Place the tablet on the tongue and allow it to disintegrate, with or without water, until the particles can be swallowed.
  - The tablet typically disintegrates in less than 1 minute.
  - Alternatively, for children or other patients who have difficulty swallowing tablets, PREVACID SoluTab can be delivered in two different ways.
    PREVACID SoluTab – Oral Syringe
    For administration via oral syringe, PREVACID SoluTab can be administered as follows:
    PREVACID SoluTab – Nasogastric Tube (≥ 8 French) Administration
    For administration via a nasogastric tube, PREVACID SoluTab can be administered as follows:
    - Place a 15 mg tablet in oral syringe and draw up 4 mL of water, or place a 30 mg tablet in oral syringe and draw up 10 mL of water.
    - Shake gently to allow for a quick dispersal.
    - After the tablet has dispersed, administer the contents within 15 minutes.
    - Refill the syringe with approximately 2 mL (5 mL for the 30 mg tablet) of water, shake gently, and administer any remaining contents.

3 DOSAGE FORMS AND STRENGTHS

- 15 mg capsules are opaque, hard gelatin, colored pink and green with the TAP logo and "PREVACID 15" imprinted on the capsule.
- 30 mg capsules are opaque, hard gelatin, colored pink and black with the TAP logo and "PREVACID 30" imprinted on the capsule.
- 15 mg tablets are white to yellowish white, uncoated, colored orange to dark brown speckles with "15" debossed on one side of the tablet.
- 30 mg tablets are white to yellowish white, uncoated, colored orange to dark brown speckles with "30" debossed on one side of the tablet.

4 CONTRAINDICATIONS

PREVACID is contraindicated in patients with known severe hypersensitivity to any component of the formulation of PREVACID. For information on contraindications for amoxicillin or clarithromycin, refer to their full prescribing information, CONTRAINDICATIONS sections.

5 WARNINGS AND PRECAUTIONS

5.1 Gastric Malignancy

Symptomatic response to therapy with lansoprazole does not preclude the presence of gastric malignancy.

5.2 Bone Fracture

Several published observational studies suggest that proton pump inhibitor (PPI) therapy may be associated with an increased risk for osteoporosis-related fractures of the hip, wrist or spine. The risk of fracture was increased in patients who received high-dose, defined as multiple daily doses, and long-term PPI therapy (a year or longer). Patients should use the lowest dose and shortest duration of PPI therapy appropriate to the condition being treated. Patients at risk for osteoporosis-related fractures should be managed according to established treatment guidelines [see Dosage and Administration (2) and Adverse Reactions (6.2)].

For information on warnings and precautions for amoxicillin or clarithromycin, refer to their full prescribing information, WARNINGS and PRECAUTIONS sections.

6 ADVERSE REACTIONS

6.1 Clinical

Worldwide, over 10,000 patients have been treated with PREVACID in Phase 2 or Phase 3 clinical trials involving various dosages and durations of treatment. In general, PREVACID treatment has been well-tolerated in both short-term and long-term trials.

Because clinical trials are conducted under widely varying conditions, adverse reaction rates observed in the clinical trials of a drug cannot be directly compared to rates in the clinical trials of another drug and may not reflect the rates observed in clinical practice.

The following adverse reactions were reported by the treating physician to have a possible or probable relationship to drug in 1% or more of PREVACID-treated patients and occurred at a greater rate in PREVACID-treated patients than placebo-treated patients in Table 1.

Table 1: Incidence of Possibly or Probably Treatment-Related Adverse Reactions in Short-Term, Placebo-Controlled PREVACID Studies
Body System/Adverse Event | PREVACID (N= 2768) % | Placebo (N= 1023) %
Body as a Whole
Abdominal Pain | 2.1 | 1.2
Digestive System
Constipation | 1.0 | 0.4
Diarrhea | 3.8 | 2.3
Nausea | 1.3 | 1.2

Headache was also seen at greater than 1% incidence but was more common on placebo. The incidence of diarrhea was similar between patients who received placebo and patients who received 15 mg and 30 mg of PREVACID, but higher in the patients who received 60 mg of PREVACID (2.9%, 1.4%, 4.2%, and 7.4%, respectively).

The most commonly reported possibly or probably treatment-related adverse event during maintenance therapy was diarrhea.

In the risk reduction study of PREVACID for NSAID-associated gastric ulcers, the incidence of diarrhea for patients treated with PREVACID, misoprostol, and placebo was 5%, 22%, and 3%, respectively.

Another study for the same indication, where patients took either a COX-2 inhibitor or lansoprazole and naproxen, demonstrated that the safety profile was similar to the prior study. Additional reactions from this study not previously observed in other clinical trials with PREVACID included contusion, duodenitis, epigastric discomfort, esophageal disorder, fatigue, hunger, hiatal hernia, hoarseness, impaired gastric emptying, metaplasia, and renal impairment.

Additional adverse experiences occurring in less than 1% of patients or subjects who received PREVACID in domestic trials are shown below:

Body as a Whole – abdomen enlarged, allergic reaction, asthenia, back pain, candidiasis, carcinoma, chest pain (not otherwise specified), chills, edema, fever, flu syndrome, halitosis, infection (not otherwise specified), malaise, neck pain, neck rigidity, pain, pelvic pain

Cardiovascular System – angina, arrhythmia, bradycardia, cerebrovascular accident/cerebral infarction, hypertension/hypotension, migraine, myocardial infarction, palpitations, shock (circulatory failure), syncope, tachycardia, vasodilation

Digestive System – abnormal stools, anorexia, bezoar, cardiospasm, cholelithiasis, colitis, dry mouth, dyspepsia, dysphagia, enteritis, eructation, esophageal stenosis, esophageal ulcer, esophagitis, fecal discoloration, flatulence, gastric nodules/fundic gland polyps, gastritis, gastroenteritis, gastrointestinal anomaly, gastrointestinal disorder, gastrointestinal hemorrhage, glossitis, gum hemorrhage, hematemesis, increased appetite, increased salivation, melena, mouth ulceration, nausea and vomiting, nausea and vomiting and diarrhea, gastrointestinal moniliasis, rectal disorder, rectal hemorrhage, stomatitis, tenesmus, thirst, tongue disorder, ulcerative colitis, ulcerative stomatitis

Endocrine System – diabetes mellitus, goiter, hypothyroidism

Hemic and Lymphatic System – anemia, hemolysis, lymphadenopathy

Metabolic and Nutritional Disorders – avitaminosis, gout, dehydration, hyperglycemia/hypoglycemia, peripheral edema, weight gain/loss

Musculoskeletal System – arthralgia, arthritis, bone disorder, joint disorder, leg cramps, musculoskeletal pain, myalgia, myasthenia, ptosis, synovitis

Nervous System – abnormal dreams, agitation, amnesia, anxiety, apathy, confusion, convulsion, dementia, depersonalization, depression, diplopia, dizziness, emotional lability, hallucinations, hemiplegia, hostility aggravated, hyperkinesia, hypertonia, hypesthesia, insomnia, libido decreased/increased, nervousness, neurosis, paresthesia, sleep disorder, somnolence, thinking abnormality, tremor, vertigo

Respiratory System – asthma, bronchitis, cough increased, dyspnea, epistaxis, hemoptysis, hiccup, laryngeal neoplasia, lung fibrosis, pharyngitis, pleural disorder, pneumonia, respiratory disorder, upper respiratory inflammation/infection, rhinitis, sinusitis, stridor

Skin and Appendages – acne, alopecia, contact dermatitis, dry skin, fixed eruption, hair disorder, maculopapular rash, nail disorder, pruritus, rash, skin carcinoma, skin disorder, sweating, urticaria

Special Senses – abnormal vision, amblyopia, blepharitis, blurred vision, cataract, conjunctivitis, deafness, dry eyes, ear/eye disorder, eye pain, glaucoma, otitis media, parosmia, photophobia, retinal degeneration/disorder, taste loss, taste perversion, tinnitus, visual field defect

Urogenital System – abnormal menses, breast enlargement, breast pain, breast tenderness, dysmenorrhea, dysuria, gynecomastia, impotence, kidney calculus, kidney pain, leukorrhea, menorrhagia, menstrual disorder, penis disorder, polyuria, testis disorder, urethral pain, urinary frequency, urinary retention, urinary tract infection, urinary urgency, urination impaired, vaginitis.

6.2 Postmarketing Experience

Additional adverse experiences have been reported since PREVACID has been marketed. The majority of these cases are foreign-sourced and a relationship to PREVACID has not been established. Because these reactions were reported voluntarily from a population of unknown size, estimates of frequency cannot be made. These events are listed below by COSTART body system.

Body as a Whole - anaphylactic/anaphylactoid reactions; Digestive System - hepatotoxicity, pancreatitis, vomiting; Hemic and Lymphatic System - agranulocytosis, aplastic anemia, hemolytic anemia, leukopenia, neutropenia, pancytopenia, thrombocytopenia, and thrombotic thrombocytopenic purpura; Musculoskeletal System – bone fracture, myositis; Skin and Appendages - severe dermatologic reactions including erythema multiforme, Stevens-Johnson syndrome, toxic epidermal necrolysis (some fatal); Special Senses - speech disorder; Urogenital System - interstitial nephritis, urinary retention.

6.3 Combination Therapy with Amoxicillin and Clarithromycin

In clinical trials using combination therapy with PREVACID plus amoxicillin and clarithromycin, and PREVACID plus amoxicillin, no adverse reactions peculiar to these drug combinations were observed. Adverse reactions that have occurred have been limited to those that had been previously reported with PREVACID, amoxicillin, or clarithromycin.

Triple Therapy: PREVACID/amoxicillin/clarithromycin

The most frequently reported adverse reactions for patients who received triple therapy for 14 days were diarrhea (7%), headache (6%), and taste perversion (5%). There were no statistically significant differences in the frequency of reported adverse reactions between the 10- and 14-day triple therapy regimens. No treatment-emergent adverse reactions were observed at significantly higher rates with triple therapy than with any dual therapy regimen.

Dual Therapy: PREVACID/amoxicillin

The most frequently reported adverse reactions for patients who received PREVACID three times daily plus amoxicillin three times daily dual therapy were diarrhea (8%) and headache (7%). No treatment-emergent adverse reactions were observed at significantly higher rates with PREVACID three times daily plus amoxicillin three times daily dual therapy than with PREVACID alone.

For information on adverse reactions with amoxicillin or clarithromycin, refer to their full prescribing information, ADVERSE REACTIONS sections.

6.4 Laboratory Values

The following changes in laboratory parameters in patients who received PREVACID were reported as adverse reactions:

Abnormal liver function tests, increased SGOT (AST), increased SGPT (ALT), increased creatinine, increased alkaline phosphatase, increased globulins, increased GGTP, increased/decreased/abnormal WBC, abnormal AG ratio, abnormal RBC, bilirubinemia, blood potassium increased, blood urea increased, crystal urine present, eosinophilia, hemoglobin decreased, hyperlipemia, increased/decreased electrolytes, increased/decreased cholesterol, increased glucocorticoids, increased LDH, increased/decreased/abnormal platelets, increased gastrin levels and positive fecal occult blood. Urine abnormalities such as albuminuria, glycosuria, and hematuria were also reported. Additional isolated laboratory abnormalities were reported.

In the placebo controlled studies, when SGOT (AST) and SGPT (ALT) were evaluated, 0.4% (4/978) and 0.4% (11/2677) patients, who received placebo and PREVACID, respectively, had enzyme elevations greater than three times the upper limit of normal range at the final treatment visit. None of these patients who received PREVACID reported jaundice at any time during the study.

In clinical trials using combination therapy with PREVACID plus amoxicillin and clarithromycin, and PREVACID plus amoxicillin, no increased laboratory abnormalities particular to these drug combinations were observed.

For information on laboratory value changes with amoxicillin or clarithromycin, refer to their full prescribing information, ADVERSE REACTIONS sections.

7 DRUG INTERACTIONS

Drugs with pH-Dependent Absorption Kinetics

PREVACID causes long-lasting inhibition of gastric acid secretion. PREVACID and other PPIs are likely to substantially decrease the systemic concentrations of the HIV protease inhibitor atazanavir, which is dependent upon the presence of gastric acid for absorption, and may result in a loss of therapeutic effect of atazanavir and the development of HIV resistance. Therefore, PREVACID and other PPIs should not be co-administered with atazanavir [see Clinical Pharmacology (12.5)].

It is theoretically possible that PREVACID and other PPIs may interfere with the absorption of other drugs where gastric pH is an important determinant of oral bioavailability (e.g., ampicillin esters, digoxin, iron salts, ketoconazole) [see Clinical Pharmacology (12.5)].

Warfarin

In a study of healthy subjects, co-administration of single or multiple 60 mg doses of PREVACID and warfarin did not affect the pharmacokinetics of warfarin nor prothrombin time [see Clinical Pharmacology (12.5)]. However, there have been reports of increased INR and prothrombin time in patients receiving PPIs and warfarin concomitantly. Increases in INR and prothrombin time may lead to abnormal bleeding and even death. Patients treated with PPIs and warfarin concomitantly may need to be monitored for increases in INR and prothrombin time [see Clinical Pharmacology (12.5)].

Tacrolimus

Concomitant administration of lansoprazole and tacrolimus may increase whole blood levels of tacrolimus, especially in transplant patients who are intermediate or poor metabolizers of CYP2C19.

Theophylline

A minor increase (10%) in the clearance of theophylline was observed following the administration of PREVACID concomitantly with theophylline. Although the magnitude of the effect on theophylline clearance is small, individual patients may require additional titration of their theophylline dosage when PREVACID is started or stopped to ensure clinically effective blood levels [see Clinical Pharmacology (12.5)].

For information on drug interactions for amoxicillin or clarithromycin, refer to their full prescribing information, DRUG INTERACTIONS sections.

8 USE IN SPECIFIC POPULATIONS

8.1 Pregnancy

Teratogenic effects

Pregnancy Category B. Reproduction studies have been performed in pregnant rats at oral doses up to 40 times the recommended human dose and in pregnant rabbits at oral doses up to 16 times the recommended human dose and have revealed no evidence of impaired fertility or harm to the fetus due to lansoprazole. There are, however, no adequate or well-controlled studies in pregnant women. Because animal reproduction studies are not always predictive of human response, this drug should be used during pregnancy only if clearly needed [see Nonclinical Toxicology (13.2)].

See full prescribing information for clarithromycin before using in pregnant women.

8.3 Nursing Mothers

Lansoprazole or its metabolites are excreted in the milk of rats. It is not known whether lansoprazole is excreted in human milk. Because many drugs are excreted in human milk, because of the potential for serious adverse reactions in nursing infants from lansoprazole, and because of the potential for tumorigenicity shown for lansoprazole in rat carcinogenicity studies, a decision should be made whether to discontinue nursing or to discontinue lansoprazole, taking into account the importance of lansoprazole to the mother.

8.4 Pediatric Use

The safety and effectiveness of PREVACID have been established in pediatric patients 1 to 17 years of age for short-term treatment of symptomatic GERD and erosive esophagitis, however, PREVACID was not effective in patients with symptomatic GERD 1 month to less than 1 year of age in a multicenter, double-blind, placebo controlled study.

Neonate to less than 1 year of age

The pharmacokinetics of lansoprazole were studied in pediatric patients with GERD aged less than 28 days and 1 to 11 months. Compared to healthy adults receiving 30 mg, neonates had higher exposure (mean weight-based normalized AUC values 2.04- and 1.88-fold higher at doses of 0.5 mg/kg/day and 1 mg/kg/day, respectively). Infants aged ≤10 weeks had clearance and exposure values that were similar to neonates. Infants aged greater than 10 weeks who received 1 mg/kg/day had mean AUC values that were similar to adults who received a 30 mg dose.

Lansoprazole was not found to be effective in a U.S. and Polish 4 week multicenter, double-blind, placebo-controlled, parallel-group study of 162 patients between one month and less than 12 months of age with symptomatic GERD based on a medical history of crying/fussing/irritability associated with feedings who had not responded to conservative GERD management (i.e., non-pharmacologic intervention) for 7 to 14 days. Patients received lansoprazole as a suspension daily (0.2 to 0.3 mg/kg/day in infants ≤10 weeks of age or 1.0 to 1.5 mg/kg/day in infants greater than 10 weeks or placebo) for up to 4 weeks of double-blind treatment.

The primary efficacy endpoint was assessed by greater than 50% reduction from baseline in either the percent of feedings with a crying/fussing/irritability episode or the duration (minutes) of a crying/fussing/irritability episode within one hour after feeding.

There was no difference in the percentage of responders between the lansoprazole pediatric suspension group and placebo group (54% in both groups).

There were no adverse events reported in pediatric clinical studies (1 month to less than 12 months of age) that were not previously observed in adults.

Based on the results of the Phase 3 efficacy study, lansoprazole was not shown to be effective. Therefore, these results do not support the use of lansoprazole in treating symptomatic GERD in infants.

One to 11 years of age

In an uncontrolled, open-label, U.S. multicenter study, 66 pediatric patients (1 to 11 years of age) with GERD were assigned, based on body weight, to receive an initial dose of either PREVACID 15 mg daily if ≤30 kg or PREVACID 30 mg daily if greater than 30 kg administered for 8 to 12 weeks. The PREVACID dose was increased (up to 30 mg twice daily) in 24 of 66 pediatric patients after 2 or more weeks of treatment if they remained symptomatic. At baseline 85% of patients had mild to moderate overall GERD symptoms (assessed by investigator interview), 58% had non-erosive GERD and 42% had erosive esophagitis (assessed by endoscopy).

After 8 to 12 weeks of PREVACID treatment, the intent-to-treat analysis demonstrated an approximate 50% reduction in frequency and severity of GERD symptoms.

Twenty-one of 27 erosive esophagitis patients were healed at 8 weeks and 100% of patients were healed at 12 weeks by endoscopy (Table 2).

Table 2: GERD Symptom Improvement and Erosive Esophagitis Healing Rates in Pediatric Patients Age 1 to 11
GERD | Final Visit [At Week 8 or Week 12] % (n/N)
Symptomatic GERD Improvement in Overall GERD Symptoms [Symptoms assessed by patients diary kept by caregiver.] | 76% (47/62 [No data were available for 4 pediatric patients.])
Erosive Esophagitis Improvement in Overall GERD Symptoms Healing Rate | 81% (22/27) 100% (27/27)

In a study of 66 pediatric patients in the age group 1 year to 11 years old after treatment with PREVACID given orally in doses of 15 mg daily to 30 mg twice daily, increases in serum gastrin levels were similar to those observed in adult studies. Median fasting serum gastrin levels increased 89% from 51 pg/mL at baseline to 97 pg/mL [interquartile range (25th to 75th percentile) of 71 to 130 pg/mL] at the final visit.

The pediatric safety of PREVACID Delayed-Release Capsules has been assessed in 66 pediatric patients aged 1 to 11 years of age. Of the 66 patients with GERD 85% (56/66) took PREVACID for 8 weeks and 15% (10/66) took it for 12 weeks.

The most frequently reported (2 or more patients) treatment-related adverse reactions in patients 1 to 11 years of age (N=66) were constipation (5%) and headache (3%).

Twelve to 17 years of age

In an uncontrolled, open-label, U.S. multicenter study, 87 adolescent patients (12 to 17 years of age) with symptomatic GERD were treated with PREVACID for 8 to 12 weeks. Baseline upper endoscopies classified these patients into two groups: 64 (74%) nonerosive GERD and 23 (26%) erosive esophagitis (EE). The nonerosive GERD patients received PREVACID 15 mg daily for 8 weeks and the EE patients received PREVACID 30 mg daily for 8 to 12 weeks. At baseline, 89% of these patients had mild to moderate overall GERD symptoms (assessed by investigator interviews). During 8 weeks of PREVACID treatment, adolescent patients experienced a 63% reduction in frequency and a 69% reduction in severity of GERD symptoms based on diary results.

Twenty-one of 22 (95.5%) adolescent erosive esophagitis patients were healed after 8 weeks of PREVACID treatment. One patient remained unhealed after 12 weeks of treatment (Table 3).

Table 3: GERD Symptom Improvement and Erosive Esophagitis Healing Rates in Pediatric Patients Age 12 to 17
GERD | Final Visit % (n/N)
Symptomatic GERD (All Patients)
Improvement in Overall GERD Symptoms [Symptoms assessed by patient diary (parents/caregivers as necessary).] | 73.2% (60/82) [No data available for 5 patients.]
Nonerosive GERD
Improvement in Overall GERD Symptoms | 71.2% (42/59)
Erosive Esophagitis
Improvement in Overall GERD Symptoms | 78.3% (18/23)
Healing Rate [Data from one healed patient was excluded from this analysis due to timing of final endoscopy.] | 95.5% (21/22)

In these 87 adolescent patients, increases in serum gastrin levels were similar to those observed in adult studies, median fasting serum gastrin levels increased 42% from 45 pg/mL at baseline to 64 pg/mL [interquartile range (25th to 75th percentile) of 44 to 88 pg/mL] at the final visit. (Normal serum gastrin levels are 25 to 111 pg/mL.)

The safety of PREVACID Delayed-Release Capsules has been assessed in these 87 adolescent patients. Of the 87 adolescent patients with GERD, 6% (5/87) took PREVACID for less than 6 weeks, 93% (81/87) for 6 to 10 weeks, and 1% (1/87) for greater than 10 weeks.

The most frequently reported (at least 3%) treatment-related adverse reactions in these patients were headache (7%), abdominal pain (5%), nausea (3%) and dizziness (3%). Treatment-related dizziness, reported in this package insert as occurring in less than 1% of adult patients, was reported in this study by 3 adolescent patients with nonerosive GERD, who had dizziness concurrently with other reactions (such as migraine, dyspnea, and vomiting).

8.5 Geriatric Use

No dosage adjustment of PREVACID is necessary in geriatric patients. The incidence rates of PREVACID-associated adverse reactions and laboratory test abnormalities are similar to those seen in younger patients [see Clinical Pharmacology (12.4)].

8.6 Renal Impairment

No dosage adjustment of PREVACID is necessary in patients with renal impairment. The pharmacokinetics of lansoprazole in patients with various degrees of renal impairment were not substantially different compared to those in subjects with normal renal function [see Clinical Pharmacology (12.4)].

8.7 Hepatic Impairment

In patients with various degrees of chronic hepatic impairment, an increase in the mean AUC of up to 500% was observed at steady state compared to healthy subjects. Consider dose reduction in patients with severe hepatic impairment [see Clinical Pharmacology (12.4)].

8.8 Gender

Over 4,000 women were treated with PREVACID. Ulcer healing rates in females were similar to those in males. The incidence rates of adverse reactions in females were similar to those seen in males [see Clinical Pharmacology (12.4)].

8.9 Race

The pooled mean pharmacokinetic parameters of PREVACID from twelve U.S. Phase 1 studies (N=513) were compared to the mean pharmacokinetic parameters from two Asian studies (N=20). The mean AUCs of PREVACID in Asian subjects were approximately twice those seen in pooled U.S. data; however, the inter-individual variability was high. The Cmax values were comparable.

10 OVERDOSAGE

PREVACID is not removed from the circulation by hemodialysis. In one reported overdose, a patient consumed 600 mg of PREVACID with no adverse reaction. Oral PREVACID doses up to 5000 mg/kg in rats [approximately 1300 times the 30 mg human dose based on body surface area (BSA)] and in mice (about 675.7 times the 30 mg human dose based on BSA) did not produce deaths or any clinical signs.

11 DESCRIPTION

The active ingredient in PREVACID Delayed-Release Capsules and PREVACID SoluTab Delayed-Release Orally Disintegrating Tablets is lansoprazole, a substituted benzimidazole, 2-[[[3-methyl-4-(2,2,2-trifluoroethoxy)-2-pyridyl] methyl] sulfinyl] benzimidazole, a compound that inhibits gastric acid secretion. Its empirical formula is C16H14F3N3O2S with a molecular weight of 369.37. PREVACID has the following structure:

Lansoprazole is a white to brownish-white odorless crystalline powder which melts with decomposition at approximately 166°C. Lansoprazole is freely soluble in dimethylformamide; soluble in methanol; sparingly soluble in ethanol; slightly soluble in ethyl acetate, dichloromethane and acetonitrile; very slightly soluble in ether; and practically insoluble in hexane and water.

Lansoprazole is stable when exposed to light for up to two months. The rate of degradation of the compound in aqueous solution increases with decreasing pH. The degradation half-life of the drug substance in aqueous solution at 25°C is approximately 0.5 hour at pH 5.0 and approximately 18 hours at pH 7.0.

PREVACID is supplied in delayed-release capsules and in delayed-release orally disintegrating tablets for oral administration.

The delayed-release capsules are available in two dosage strengths: 15 mg and 30 mg of lansoprazole per capsule. Each delayed-release capsule contains enteric-coated granules consisting of 15 mg or 30 mg of lansoprazole (active ingredient) and the following inactive ingredients: sugar sphere, sucrose, methacrylic acid copolymer, low substituted hydroxypropyl cellulose, starch, magnesium carbonate, talc, polyethylene glycol, titanium dioxide, polysorbate 80, hydroxypropyl cellulose, colloidal silicon dioxide, D&C Red No. 28, FD&C Blue No. 1, FD&C Green No. 3 [PREVACID 15-mg capsules only.] , and FD&C Red No. 40.

PREVACID SoluTab Delayed-Release Orally Disintegrating Tablets are available in two dosage strengths: 15 mg and 30 mg of lansoprazole per tablet. Each delayed-release orally disintegrating tablet contains enteric-coated microgranules consisting of 15 mg or 30 mg of lansoprazole (active ingredient) and the following inactive ingredients: mannitol, methacrylic acid, hydroxypropyl cellulose, lactose monohydrate-microcrystalline cellulose sphere, triethyl citrate, crospovidone, polyacrylate, magnesium carbonate, aspartame [Phenylketonurics: Contains Phenylalanine 2.5 mg per 15 mg Tablet and 5.1 mg per 30 mg Tablet.] , glyceryl monostearate, hypromellose, magnesium stearate, citric acid, titanium dioxide, talc, artificial strawberry flavor, polyethylene glycol, polysorbate 80 and ferric oxide.

12 CLINICAL PHARMACOLOGY

12.1 Mechanism of Action

PREVACID (lansoprazole) belongs to a class of antisecretory compounds, the substituted benzimidazoles, that suppress gastric acid secretion by specific inhibition of the (H^+, K^+)-ATPase enzyme system at the secretory surface of the gastric parietal cell. Because this enzyme system is regarded as the acid (proton) pump within the parietal cell, lansoprazole has been characterized as a gastric acid-pump inhibitor, in that it blocks the final step of acid production. This effect is dose-related and leads to inhibition of both basal and stimulated gastric acid secretion irrespective of the stimulus. Lansoprazole does not exhibit anticholinergic or histamine type-2 antagonist activity.

12.2 Pharmacodynamics

Antisecretory Activity: After oral administration, lansoprazole was shown to significantly decrease the basal acid output and significantly increase the mean gastric pH and percent of time the gastric pH was greater than 3 and greater than 4. Lansoprazole also significantly reduced meal-stimulated gastric acid output and secretion volume, as well as pentagastrin-stimulated acid output. In patients with hypersecretion of acid, lansoprazole significantly reduced basal and pentagastrin-stimulated gastric acid secretion. Lansoprazole inhibited the normal increases in secretion volume, acidity and acid output induced by insulin.

The intragastric pH results of a five-day, pharmacodynamic, crossover study of 15 mg and 30 mg of once daily lansoprazole are presented in Table 4:

Table 4: Mean Antisecretory Effects After Single and Multiple Daily PREVACID Dosing
 |  | PREVACID
Parameter | Baseline Value | 15 mg |  | 30 mg
Parameter | Baseline Value | Day 1 | Day 5 | Day 1 | Day 5
Mean 24 Hour pH | 2.1 | 2.7 [(p<0.05) versus baseline only.] | 4.0 | 3.6 [(p<0.05) versus baseline and lansoprazole 15 mg.] | 4.9
Mean Nighttime pH | 1.9 | 2.4 | 3.0 | 2.6 | 3.8
% Time Gastric pH>3 | 18 | 33 | 59 | 51 | 72
% Time Gastric pH>4 | 12 | 22 | 49 | 41 | 66
NOTE: An intragastric pH of greater than 4 reflects a reduction in gastric acid by 99%.

After the initial dose in this study, increased gastric pH was seen within 1 to 2 hours with 30 mg of lansoprazole and 2 to 3 hours with 15 mg of lansoprazole. After multiple daily dosing, increased gastric pH was seen within the first hour post-dosing with 30 mg of lansoprazole and within 1 to 2 hours post-dosing with 15 mg of lansoprazole.

Acid suppression may enhance the effect of antimicrobials in eradicating Helicobacter pylori (H. pylori). The percentage of time gastric pH was elevated above 5 and 6 was evaluated in a crossover study of PREVACID given daily, twice daily and three times daily (Table 5).

Table 5: Mean Antisecretory Effects After 5 Days of Twice Daily and Three Times Daily Dosing
 | PREVACID
Parameter | 30 mg daily | 15 mg twice daily | 30 mg twice daily | 30 mg three times daily
% Time Gastric pH>5 | 43 | 47 | 59 [(p<0.05) versus PREVACID 30 mg daily] | 77 [(p<0.05) versus PREVACID 30 mg daily, 15 mg twice daily and 30 mg twice daily.]
% Time Gastric pH>6 | 20 | 23 | 28 | 45

The inhibition of gastric acid secretion as measured by intragastric pH gradually returned to normal over two to four days after multiple doses. There was no indication of rebound gastric acidity.

Enterochromaffin-like (ECL) Cell Effects

During lifetime exposure of rats with up to 150 mg/kg/day of lansoprazole dosed seven days per week, marked hypergastrinemia was observed followed by ECL cell proliferation and formation of carcinoid tumors, especially in female rats. Gastric biopsy specimens from the body of the stomach from approximately 150 patients treated continuously with lansoprazole for at least one year did not show evidence of ECL cell effects similar to those seen in rat studies. Longer term data are needed to rule out the possibility of an increased risk of the development of gastric tumors in patients receiving long-term therapy with lansoprazole [see Nonclinical Toxicology (13.1)].

Other Gastric Effects in Humans

Lansoprazole did not significantly affect mucosal blood flow in the fundus of the stomach. Due to the normal physiologic effect caused by the inhibition of gastric acid secretion, a decrease of about 17% in blood flow in the antrum, pylorus, and duodenal bulb was seen. Lansoprazole significantly slowed the gastric emptying of digestible solids. Lansoprazole increased serum pepsinogen levels and decreased pepsin activity under basal conditions and in response to meal stimulation or insulin injection. As with other agents that elevate intragastric pH, increases in gastric pH were associated with increases in nitrate-reducing bacteria and elevation of nitrite concentration in gastric juice in patients with gastric ulcer. No significant increase in nitrosamine concentrations was observed.

Serum Gastrin Effects

In over 2100 patients, median fasting serum gastrin levels increased 50% to 100% from baseline but remained within normal range after treatment with 15 to 60 mg of oral lansoprazole. These elevations reached a plateau within two months of therapy and returned to pretreatment levels within four weeks after discontinuation of therapy.

Endocrine Effects

Human studies for up to one year have not detected any clinically significant effects on the endocrine system. Hormones studied include testosterone, luteinizing hormone (LH), follicle stimulating hormone (FSH), sex hormone binding globulin (SHBG), dehydroepiandrosterone sulfate (DHEA-S), prolactin, cortisol, estradiol, insulin, aldosterone, parathormone, glucagon, thyroid stimulating hormone (TSH), triiodothyronine (T3), thyroxine (T4), and somatotropic hormone (STH). Lansoprazole in oral doses of 15 to 60 mg for up to one year had no clinically significant effect on sexual function. In addition, lansoprazole in oral doses of 15 to 60 mg for two to eight weeks had no clinically significant effect on thyroid function. In 24-month carcinogenicity studies in Sprague-Dawley rats with daily lansoprazole dosages up to 150 mg/kg, proliferative changes in the Leydig cells of the testes, including benign neoplasm, were increased compared to control rats.

Other Effects

No systemic effects of lansoprazole on the central nervous system, lymphoid, hematopoietic, renal, hepatic, cardiovascular, or respiratory systems have been found in humans. Among 56 patients who had extensive baseline eye evaluations, no visual toxicity was observed after lansoprazole treatment (up to 180 mg/day) for up to 58 months. After lifetime lansoprazole exposure in rats, focal pancreatic atrophy, diffuse lymphoid hyperplasia in the thymus, and spontaneous retinal atrophy were seen.

Microbiology

Lansoprazole, clarithromycin and/or amoxicillin have been shown to be active against most strains of Helicobacter pylori in vitro and in clinical infections as described in the INDICATIONS AND USAGE section [see Indications and Usage (1.2)].

Helicobacter pylori Pretreatment Resistance

Clarithromycin pretreatment resistance (≥2.0 mcg/mL) was 9.5% (91/960) by E-test and 11.3% (12/106) by agar dilution in the dual and triple therapy clinical trials (M93-125, M93-130, M93-131, M95-392, and M95-399).

Amoxicillin pretreatment susceptible isolates (≤0.25 mcg/mL) occurred in 97.8% (936/957) and 98.0% (98/100) of the patients in the dual and triple therapy clinical trials by E-test and agar dilution, respectively. Twenty-one of 957 patients (2.2%) by E-test, and 2 of 100 patients (2.0%) by agar dilution, had amoxicillin pretreatment MICs of greater than 0.25 mcg/mL. One patient on the 14-day triple therapy regimen had an unconfirmed pretreatment amoxicillin minimum inhibitory concentration (MIC) of greater than 256 mcg/mL by E-test and the patient was eradicated of H. pylori (Table 6).

Table 6: Clarithromycin Susceptibility Test Results and Clinical/Bacteriological Outcomes [Includes only patients with pretreatment clarithromycin susceptibility test results]
Clarithromycin Pretreatment Results |  | Clarithromycin Post-treatment Results
 |  | H. pylori negative - eradicated | H. pylori positive – not eradicated Post-treatment susceptibility results
 |  |  | S [Susceptible (S) MIC ≤0.25 mcg/mL, Intermediate (I) MIC 0.5 to 1.0 mcg/mL, Resistant (R) MIC ≥2 mcg/mL] | I | R | No MIC
Triple Therapy 14-Day (lansoprazole 30 mg twice daily/amoxicillin 1 g twice daily/clarithromycin 500 mg twice daily) (M95-399, M93-131, M95-392)
Susceptible | 112 | 105 |  |  |  | 7
Intermediate | 3 | 3
Resistant | 17 | 6 |  |  | 7 | 4
Triple Therapy 10-Day (lansoprazole 30 mg twice daily/amoxicillin 1 g twice daily/clarithromycin 500 mg twice daily) (M95-399)
Susceptible | 42 | 40 | 1 |  | 1
Intermediate
Resistant | 4 | 1 |  |  | 3

Patients not eradicated of H. pylori following lansoprazole/amoxicillin/clarithromycin triple therapy will likely have clarithromycin resistant H. pylori. Therefore, for those patients who fail therapy, clarithromycin susceptibility testing should be done when possible. Patients with clarithromycin resistant H. pylori should not be treated with lansoprazole/amoxicillin/clarithromycin triple therapy or with regimens which include clarithromycin as the sole antimicrobial agent.

Amoxicillin Susceptibility Test Results and Clinical/Bacteriological Outcomes: In the dual and triple therapy clinical trials, 82.6% (195/236) of the patients that had pretreatment amoxicillin susceptible MICs (≤0.25 mcg/mL) were eradicated of H. pylori. Of those with pretreatment amoxicillin MICs of greater than 0.25 mcg/mL, three of six had the H. pylori eradicated. A total of 30% (21/70) of the patients failed lansoprazole 30 mg three times daily/amoxicillin 1 g three times daily dual therapy and a total of 12.8% (22/172) of the patients failed the 10- and 14-day triple therapy regimens. Post-treatment susceptibility results were not obtained on 11 of the patients who failed therapy. Nine of the 11 patients with amoxicillin post-treatment MICs that failed the triple therapy regimen also had clarithromycin resistant H. pylori isolates.

Susceptibility Test for Helicobacter pylori: The reference methodology for susceptibility testing of H. pylori is agar dilution MICs.^1 One to three microliters of an inoculum equivalent to a No. 2 McFarland standard (1 × 10^7 to 1 × 10^8 CFU/mL for H. pylori) are inoculated directly onto freshly prepared antimicrobial-containing Mueller-Hinton agar plates with 5% aged defibrinated sheep blood (≥2 weeks old). The agar dilution plates are incubated at 35°C in a microaerobic environment produced by a gas generating system suitable for campylobacters.

After 3 days of incubation, the MICs are recorded as the lowest concentration of antimicrobial agent required to inhibit growth of the organism. The clarithromycin and amoxicillin MIC values should be interpreted according to the following criteria (Table 7):

Table 7
Clarithromycin MIC (mcg/mL) [These are tentative breakpoints for the agar dilution methodology and they should not be used to interpret results obtained using alternative methods.] | Interpretation
≤0.25 | Susceptible (S)
0.5-1.0 | Intermediate (I)
≥2.0 | Resistant (R)
Amoxicillin MIC (mcg/mL), [There were not enough organisms with MICs greater than 0.25 mcg/mL to determine a resistance breakpoint.] | Interpretation
≤0.25 | Susceptible (S)

Standardized susceptibility test procedures require the use of laboratory control microorganisms to control the technical aspects of the laboratory procedures. Standard clarithromycin and amoxicillin powders should provide the following MIC values (Table 8):

Table 8
Microorganism | Antimicrobial Agent | MIC (mcg/mL) [These are quality control ranges for the agar dilution methodology and they should not be used to control test results obtained using alternative methods.]
H. pylori ATCC 43504 | Clarithromycin | 0.015-0.12
H. pylori ATCC 43504 | Amoxicillin | 0.015-0.12

12.3 Pharmacokinetics

PREVACID Delayed-Release Capsules and PREVACID SoluTab Delayed-Release Orally Disintegrating Tablets contain an enteric-coated granule formulation of lansoprazole. Absorption of lansoprazole begins only after the granules leave the stomach. Absorption is rapid, with mean peak plasma levels of lansoprazole occurring after approximately 1.7 hours. After a single-dose administration of 15 mg to 60 mg of oral lansoprazole, the peak plasma concentrations (Cmax) of lansoprazole and the area under the plasma concentration curves (AUCs) of lansoprazole were approximately proportional to the administered dose. Lansoprazole does not accumulate and its pharmacokinetics are unaltered by multiple dosing.

Absorption: The absorption of lansoprazole is rapid, with the mean Cmax occurring approximately 1.7 hours after oral dosing, and the absolute bioavailability is over 80%. In healthy subjects, the mean (±SD) plasma half-life was 1.5 (±1.0) hours. Both the Cmax and AUC are diminished by about 50% to 70% if lansoprazole is given 30 minutes after food, compared to the fasting condition. There is no significant food effect if lansoprazole is given before meals.

Distribution: Lansoprazole is 97% bound to plasma proteins. Plasma protein binding is constant over the concentration range of 0.05 to 5.0 mcg/mL.

Metabolism: Lansoprazole is extensively metabolized in the liver. Two metabolites have been identified in measurable quantities in plasma (the hydroxylated sulfinyl and sulfone derivatives of lansoprazole). These metabolites have very little or no antisecretory activity. Lansoprazole is thought to be transformed into two active species which inhibit acid secretion by blocking the proton pump [(H^+, K^+)-ATPase enzyme system] at the secretory surface of the gastric parietal cell. The two active species are not present in the systemic circulation. The plasma elimination half-life of lansoprazole is less than 2 hours while the acid inhibitory effect lasts more than 24 hours. Therefore, the plasma elimination half-life of lansoprazole does not reflect its duration of suppression of gastric acid secretion.

Elimination: Following single-dose oral administration of PREVACID, virtually no unchanged lansoprazole was excreted in the urine. In one study, after a single oral dose of ^14C-lansoprazole, approximately one-third of the administered radiation was excreted in the urine and two-thirds was recovered in the feces. This implies a significant biliary excretion of the lansoprazole metabolites.

12.4 Specific Populations

Pediatric Use:

One to 17 years of age

The pharmacokinetics of lansoprazole were studied in pediatric patients with GERD aged 1 to 11 years and 12 to 17 years in two separate clinical studies. In children aged 1 to 11 years, lansoprazole was dosed 15 mg daily for subjects weighing ≤30 kg and 30 mg daily for subjects weighing greater than 30 kg. Mean Cmax and AUC values observed on Day 5 of dosing were similar between the two dose groups and were not affected by weight or age within each weight-adjusted dose group used in the study. In adolescent subjects aged 12 to 17 years, subjects were randomized to receive lansoprazole at 15 mg or 30 mg daily. Mean Cmax and AUC values of lansoprazole were not affected by body weight or age; and nearly dose-proportional increases in mean Cmax and AUC values were observed between the two dose groups in the study. Overall, lansoprazole pharmacokinetics in pediatric patients aged 1 to 17 years were similar to those observed in healthy adult subjects.

Neonate to less than one year of age

Refer to Section 8.4 for the pharmacokinetics of lansoprazole in pediatric patients with GERD aged less than 28 days and 1 to 11 months.

Geriatric Use: The clearance of lansoprazole is decreased in the elderly, with elimination half-life increased approximately 50% to 100%. Because the mean half-life in the elderly remains between 1.9 to 2.9 hours, repeated once daily dosing does not result in accumulation of lansoprazole. Peak plasma levels were not increased in the elderly. No dosage adjustment is necessary in the elderly [see Use in Specific Populations (8.5)].

Renal Impairment: In patients with severe renal impairment, plasma protein binding decreased by 1.0% to 1.5% after administration of 60 mg of lansoprazole. Patients with renal impairment had a shortened elimination half-life and decreased total AUC (free and bound). The AUC for free lansoprazole in plasma, however, was not related to the degree of renal impairment; and the Cmax and Tmax (time to reach the maximum concentration) were not different than the Cmax and Tmax from subjects with normal renal function. No dosage adjustment is necessary in patients with renal impairment [see Use in Specific Populations (8.6)].

Hepatic Impairment: In patients with various degrees of chronic hepatic impairment, the mean plasma half-life of lansoprazole was prolonged from 1.5 hours to 3.2 to 7.2 hours. An increase in the mean AUC of up to 500% was observed at steady state in hepatically-impaired patients compared to healthy subjects. Consider dose reduction in patients with severe hepatic impairment [see Use in Specific Populations (8.7)].

Gender: In a study comparing 12 male and 6 female human subjects who received lansoprazole, no gender differences were found in pharmacokinetics and intragastric pH results [see Use in Specific Populations (8.5)].

12.5 Drug-Drug Interactions

It is theoretically possible that PREVACID may interfere with the absorption of other drugs where gastric pH is an important determinant of bioavailability (e.g., ketoconazole, ampicillin esters, iron salts, digoxin).

PREVACID is metabolized through the cytochrome P450 system, specifically through the CYP3A and CYP2C19 isozymes. Studies have shown that PREVACID does not have clinically significant interactions with other drugs metabolized by the cytochrome P450 system, such as warfarin, antipyrine, indomethacin, ibuprofen, phenytoin, propranolol, prednisone, diazepam, or clarithromycin in healthy subjects. These compounds are metabolized through various cytochrome P450 isozymes including CYP1A2, CYP2C9, CYP2C19, CYP2D6, and CYP3A.

Atazanavir: PREVACID causes long-lasting inhibition of gastric acid secretion. PREVACID substantially decreases the systemic concentrations of the HIV protease inhibitor atazanavir, which is dependent upon the presence of gastric acid for absorption, and may result in a loss of therapeutic effect of atazanavir and the development of HIV resistance. Therefore, PREVACID, or other proton pump inhibitors, should not be co-administered with atazanavir.

Theophylline: When PREVACID was administered concomitantly with theophylline (CYP1A2, CYP3A), a minor increase (10%) in the clearance of theophylline was seen. Because of the small magnitude and the direction of the effect on theophylline clearance, this interaction is unlikely to be of clinical concern. Nonetheless, individual patients may require additional titration of their theophylline dosage when PREVACID is started or stopped to ensure clinically effective blood levels.

Warfarin: In a study of healthy subjects neither the pharmacokinetics of warfarin enantiomers nor prothrombin time were affected following single or multiple 60 mg doses of lansoprazole. However, there have been reports of increased International Normalized Ratio (INR) and prothrombin time in patients receiving proton pump inhibitors, including PREVACID, and warfarin concomitantly. Increases in INR and prothrombin time may lead to abnormal bleeding and even death. Patients treated with proton pump inhibitors and warfarin concomitantly may need to be monitored for increases in INR and prothrombin time.

Methotrexate and 7-hydromethotrexate: In an open-label, single-arm, eight-day, pharmacokinetic study of 28 adult rheumatoid arthritis patients (who required the chronic use of 7.5 to 15 mg of methotrexate given weekly), administration of 7 days of naproxen 500 mg twice daily and PREVACID 30 mg daily had no effect on the pharmacokinetics of methotrexate and 7-hydroxymethotrexate. While this study was not designed to assess the safety of this combination of drugs, no major adverse reactions were noted.

Amoxicillin: PREVACID has also been shown to have no clinically significant interaction with amoxicillin.

Sucralfate: In a single-dose crossover study examining PREVACID 30 mg and omeprazole 20 mg each administered alone and concomitantly with sucralfate 1 gram, absorption of the proton pump inhibitors was delayed and their bioavailability was reduced by 17% and 16%, respectively, when administered concomitantly with sucralfate. Therefore, proton pump inhibitors should be taken at least 30 minutes prior to sucralfate. In clinical trials, antacids were administered concomitantly with PREVACID and there was no evidence of a change in the efficacy of PREVACID.

13 NONCLINICAL TOXICOLOGY

13.1 Carcinogenesis, Mutagenesis, Impairment of Fertility

In two 24-month carcinogenicity studies, Sprague-Dawley rats were treated with oral lansoprazole doses of 5 to 150 mg/kg/day, about 1 to 40 times the exposure on a body surface (mg/m^2) basis of a 50 kg person of average height [1.46 m^2 body surface area (BSA)] given the recommended human dose of 30 mg/day. Lansoprazole produced dose-related gastric enterochromaffin-like (ECL) cell hyperplasia and ECL cell carcinoids in both male and female rats. It also increased the incidence of intestinal metaplasia of the gastric epithelium in both sexes. In male rats, lansoprazole produced a dose-related increase of testicular interstitial cell adenomas. The incidence of these adenomas in rats receiving doses of 15 to 150 mg/kg/day (4 to 40 times the recommended human dose based on BSA) exceeded the low background incidence (range = 1.4 to 10%) for this strain of rat.

In a 24-month carcinogenicity study, CD-1 mice were treated with oral lansoprazole doses of 15 to 600 mg/kg/day, 2 to 80 times the recommended human dose based on BSA. Lansoprazole produced a dose-related increased incidence of gastric ECL cell hyperplasia. It also produced an increased incidence of liver tumors (hepatocellular adenoma plus carcinoma). The tumor incidences in male mice treated with 300 and 600 mg/kg/day (40 to 80 times the recommended human dose based on BSA) and female mice treated with 150 to 600 mg/kg/day (20 to 80 times the recommended human dose based on BSA) exceeded the ranges of background incidences in historical controls for this strain of mice. Lansoprazole treatment produced adenoma of rete testis in male mice receiving 75 to 600 mg/kg/day (10 to 80 times the recommended human dose based on BSA).

A 26-week p53 (+/-) transgenic mouse carcinogenicity study was not positive.

Lansoprazole was not genotoxic in the Ames test, the ex vivo rat hepatocyte unscheduled DNA synthesis (UDS) test, the in vivo mouse micronucleus test, or the rat bone marrow cell chromosomal aberration test. It was positive in in vitro human lymphocyte chromosomal aberration assays.

Lansoprazole at oral doses up to 150 mg/kg/day (40 times the recommended human dose based on BSA) was found to have no effect on fertility and reproductive performance of male and female rats.

13.2 Animal Toxicology and/or Pharmacology

Reproductive Toxicology Studies

Reproduction studies have been performed in pregnant rats at oral lansoprazole doses up to 150 mg/kg/day [40 times the recommended human dose (30 mg/day) based on body surface area (BSA)] and pregnant rabbits at oral lansoprazole doses up to 30 mg/kg/day (16 times the recommended human dose based on BSA) and have revealed no evidence of impaired fertility or harm to the fetus due to lansoprazole.

14 CLINICAL STUDIES

Duodenal Ulcer

In a U.S. multicenter, double-blind, placebo-controlled, dose-response (15, 30, and 60 mg of PREVACID once daily) study of 284 patients with endoscopically documented duodenal ulcer, the percentage of patients healed after two and four weeks was significantly higher with all doses of PREVACID than with placebo. There was no evidence of a greater or earlier response with the two higher doses compared with PREVACID 15 mg. Based on this study and the second study described below, the recommended dose of PREVACID in duodenal ulcer is 15 mg per day (Table 9).

Table 9: Duodenal Ulcer Healing Rates
 | PREVACID |  |  | Placebo
Week | 15 mg daily | 30 mg daily | 60 mg daily | Placebo
Week | (N=68) | (N=74) | (N=70) | (N=72)
2 | 42.4% [(p≤0.001) versus placebo.] | 35.6% | 39.1% | 11.3%
4 | 89.4% | 91.7% | 89.9% | 46.1%

PREVACID 15 mg was significantly more effective than placebo in relieving day and nighttime abdominal pain and in decreasing the amount of antacid taken per day.

In a second U.S. multicenter study, also double-blind, placebo-controlled, dose-comparison (15 and 30 mg of PREVACID once daily), and including a comparison with ranitidine, in 280 patients with endoscopically documented duodenal ulcer, the percentage of patients healed after four weeks was significantly higher with both doses of PREVACID than with placebo. There was no evidence of a greater or earlier response with the higher dose of PREVACID. Although the 15 mg dose of PREVACID was superior to ranitidine at 4 weeks, the lack of significant difference at 2 weeks and the absence of a difference between 30 mg of PREVACID and ranitidine leaves the comparative effectiveness of the two agents undetermined (Table 10) [see Indications and Usage (1.1)].

Table 10: Duodenal Ulcer Healing Rates
 | PREVACID |  | Ranitidine | Placebo
Week | 15 mg daily | 30 mg daily | 300 mg h.s. | Placebo
Week | (N=80) | (N=77) | (N=82) | (N=41)
2 | 35.0% | 44.2% | 30.5% | 34.2%
4 | 92.3% [(p≤0.05) versus placebo and ranitidine.] | 80.3% [(p≤0.05) versus placebo.] | 70.5% | 47.5%

H. pylori Eradication to Reduce the Risk of Duodenal Ulcer Recurrence

Randomized, double-blind clinical studies performed in the U.S. in patients with H. pylori and duodenal ulcer disease (defined as an active ulcer or history of an ulcer within one year) evaluated the efficacy of PREVACID in combination with amoxicillin capsules and clarithromycin tablets as triple 14-day therapy or in combination with amoxicillin capsules as dual 14-day therapy for the eradication of H. pylori. Based on the results of these studies, the safety and efficacy of two different eradication regimens were established:

Triple therapy: | PREVACID 30 mg twice daily/amoxicillin 1 g twice daily/clarithromycin 500 mg twice daily
Dual therapy: | PREVACID 30 mg three times daily/amoxicillin 1 g three times daily

All treatments were for 14 days. H. pylori eradication was defined as two negative tests (culture and histology) at 4 to 6 weeks following the end of treatment.

Triple therapy was shown to be more effective than all possible dual therapy combinations. Dual therapy was shown to be more effective than both monotherapies. Eradication of H. pylori has been shown to reduce the risk of duodenal ulcer recurrence.

A randomized, double-blind clinical study performed in the U.S. in patients with H. pylori and duodenal ulcer disease (defined as an active ulcer or history of an ulcer within one year) compared the efficacy of PREVACID triple therapy for 10 and 14 days. This study established that the 10-day triple therapy was equivalent to the 14-day triple therapy in eradicating H. pylori (Tables 11 and 12) [see Indications and Usage (1.2)].

Table 11
H. pylori Eradication Rates – Triple Therapy
(PREVACID/amoxicillin/clarithromycin)
Percent of Patients Cured
[95% Confidence Interval]
(Number of patients)
Study | Duration | Triple Therapy Evaluable Analysis [Based on evaluable patients with confirmed duodenal ulcer (active or within one year) and H. pylori infection at baseline defined as at least two of three positive endoscopic tests from CLOtest, histology and/or culture. Patients were included in the analysis if they completed the study. Additionally, if patients dropped out of the study due to an adverse event related to the study drug, they were included in the evaluable analysis as failures of therapy.] | Triple Therapy Intent-to-Treat Analysis [Patients were included in the analysis if they had documented H. pylori infection at baseline as defined above and had a confirmed duodenal ulcer (active or within one year). All dropouts were included as failures of therapy.]
M93-131 | 14 days | 92 [(p<0.05) versus PREVACID/amoxicillin and PREVACID/clarithromycin dual therapy.] [80.0-97.7] (N=48) | 86 [73.3-93.5] (N=55)
M95-392 | 14 days | 86 [(p<0.05) versus clarithromycin/amoxicillin dual therapy.] [75.7-93.6] (N=66) | 83 [72.0-90.8] (N=70)
M95-399 [The 95% confidence interval for the difference in eradication rates, 10-day minus 14-day is (-10.5, 8.1) in the evaluable analysis and (-9.7, 9.1) in the intent-to-treat analysis.] | 14 days | 85 [77.0-91.0] (N=113) | 82 [73.9-88.1] (N=126)
M95-399 [The 95% confidence interval for the difference in eradication rates, 10-day minus 14-day is (-10.5, 8.1) in the evaluable analysis and (-9.7, 9.1) in the intent-to-treat analysis.] | 10 days | 84 [76.0-89.8] (N=123) | 81 [73.9-87.6] (N=135)

Table 12
H. pylori Eradication Rates – 14-Day Dual Therapy
(PREVACID/amoxicillin)
Percent of Patients Cured
[95% Confidence Interval]
(Number of patients)
Study | Dual Therapy Evaluable Analysis [Based on evaluable patients with confirmed duodenal ulcer (active or within one year) and H. pylori infection at baseline defined as at least two of three positive endoscopic tests from CLOtest, histology and/or culture. Patients were included in the analysis if they completed the study. Additionally, if patients dropped out of the study due to an adverse event related to the study drug, they were included in the analysis as failures of therapy.] | Dual Therapy Intent-to-Treat Analysis [Patients were included in the analysis if they had documented H. pylori infection at baseline as defined above and had a confirmed duodenal ulcer (active or within one year). All dropouts were included as failures of therapy.]
M93-131 | 77 [(p<0.05) versus PREVACID alone.] [62.5-87.2] (N=51) | 70 [56.8-81.2] (N=60)
M93-125 | 66 [(p<0.05) versus PREVACID alone or amoxicillin alone.] [51.9-77.5] (N=58) | 61 [48.5-72.9] (N=67)

Long-Term Maintenance Treatment of Duodenal Ulcers

PREVACID has been shown to prevent the recurrence of duodenal ulcers. Two independent, double-blind, multicenter, controlled trials were conducted in patients with endoscopically confirmed healed duodenal ulcers. Patients remained healed significantly longer and the number of recurrences of duodenal ulcers was significantly less in patients treated with PREVACID than in patients treated with placebo over a 12-month period (Table 13) [see Indications and Usage (1.3)].

Table 13: Endoscopic Remission Rates
Trial | Drug | No. of Pts. | Percent in Endoscopic Remission
Trial | Drug | No. of Pts. | 0-3 mo. | 0-6 mo. | 0-12 mo.
#1 | PREVACID 15 mg daily | 86 | 90% [(p≤0.001) versus placebo.] | 87% | 84%
#1 | Placebo | 83 | 49% | 41% | 39%
#2 | PREVACID 30 mg daily | 18 | 94% | 94% | 85%
#2 | PREVACID 15 mg daily | 15 | 87% | 79% | 70%
#2 | Placebo | 15 | 33% | 0% | 0%
%=Life Table Estimate

In trial #2, no significant difference was noted between PREVACID 15 mg and 30 mg in maintaining remission.

Gastric Ulcer

In a U.S. multicenter, double-blind, placebo-controlled study of 253 patients with endoscopically documented gastric ulcer, the percentage of patients healed at four and eight weeks was significantly higher with PREVACID 15 mg and 30 mg once a day than with placebo (Table 14) [see Indications and Usage (1.4)].

Table 14: Gastric Ulcer Healing Rates
 | PREVACID |  |  | Placebo
Week | 15 mg daily | 30 mg daily | 60 mg daily | Placebo
Week | (N=65) | (N=63) | (N=61) | (N=64)
4 | 64.6% [(p≤0.05) versus placebo.] | 58.1% | 53.3% | 37.5%
8 | 92.2% | 96.8% | 93.2% | 76.7%

Patients treated with any PREVACID dose reported significantly less day and night abdominal pain along with fewer days of antacid use and fewer antacid tablets used per day than the placebo group.

Independent substantiation of the effectiveness of PREVACID 30 mg was provided by a meta-analysis of published and unpublished data.

Healing of NSAID-Associated Gastric Ulcer

In two U.S. and Canadian multicenter, double-blind, active-controlled studies in patients with endoscopically confirmed NSAID-associated gastric ulcer who continued their NSAID use, the percentage of patients healed after 8 weeks was statistically significantly higher with 30 mg of PREVACID than with the active control. A total of 711 patients were enrolled in the study, and 701 patients were treated. Patients ranged in age from 18 to 88 years (median age 59 years), with 67% female patients and 33% male patients. Race was distributed as follows: 87% Caucasian, 8% Black, 5% Other. There was no statistically significant difference between PREVACID 30 mg daily and the active control on symptom relief (i.e., abdominal pain) (Table 15) [see Indications and Usage (1.5)].

Table 15: NSAID-Associated Gastric Ulcer Healing Rates [Actual observed ulcer(s) healed at time points ± 2 days]
Study #1
 | PREVACID | Active Control [Dose for healing of gastric ulcer]
 | 30 mg daily | Active Control [Dose for healing of gastric ulcer]
Week 4 | 60% (53/88) [(p≤0.05) versus the active control] | 28% (23/83)
Week 8 | 79% (62/79) | 55% (41/74)
Study #2
 | PREVACID | Active Control
 | 30 mg daily | Active Control
Week 4 | 53% (40/75) | 38% (31/82)
Week 8 | 77% (47/61) | 50% (33/66)

Risk Reduction of NSAID-Associated Gastric Ulcer

In one large U.S., multicenter, double-blind, placebo- and misoprostol-controlled (misoprostol blinded only to the endoscopist) study in patients who required chronic use of an NSAID and who had a history of an endoscopically documented gastric ulcer, the proportion of patients remaining free from gastric ulcer at 4, 8, and 12 weeks was significantly higher with 15 or 30 mg of PREVACID than placebo. A total of 537 patients were enrolled in the study, and 535 patients were treated. Patients ranged in age from 23 to 89 years (median age 60 years), with 65% female patients and 35% male patients. Race was distributed as follows: 90% Caucasian, 6% Black, 4% other. The 30 mg dose of PREVACID demonstrated no additional benefit in risk reduction of the NSAID-associated gastric ulcer than the 15 mg dose (Table 16) [see Indications and Usage (1.6)].

Table 16: Proportion of Patients Remaining Free of Gastric Ulcers [% = Life Table Estimate]
 | PREVACID | PREVACID | Misoprostol
 | 15 mg daily | 30 mg daily | 200 mcg four times daily | Placebo
Week | (N=121) | (N=116) | (N=106) | (N=112)
4 | 90% | 92% | 96% | 66%
8 | 86% | 88% | 95% | 60%
12 | 80% | 82% | 93% | 51%
(p<0.001) PREVACID 15 mg daily versus placebo; PREVACID 30 mg daily versus placebo; and misoprostol 200 mcg four times daily versus placebo.
(p<0.05) Misoprostol 200 mcg four times daily versus PREVACID 15 mg daily; and misoprostol 200 mcg four times daily versus PREVACID 30 mg daily.

Gastroesophageal Reflux Disease (GERD)

Symptomatic GERD: In a U.S. multicenter, double-blind, placebo-controlled study of 214 patients with frequent GERD symptoms, but no esophageal erosions by endoscopy, significantly greater relief of heartburn associated with GERD was observed with the administration of lansoprazole 15 mg once daily up to 8 weeks than with placebo. No significant additional benefit from lansoprazole 30 mg once daily was observed.

The intent-to-treat analyses demonstrated significant reduction in frequency and severity of day and night heartburn. Data for frequency and severity for the 8-week treatment period are presented in Table 17 and in Figures 1 and 2:

Table 17: Frequency of Heartburn
Variable | Placebo (n=43) | PREVACID 15 mg (n=80) | PREVACID 30 mg (n=86)
Variable | Median
% of Days without Heartburn
Week 1 | 0% | 71% [(p<0.01) versus placebo.] | 46%
Week 4 | 11% | 81% | 76%
Week 8 | 13% | 84% | 82%
% of Nights without Heartburn
Week 1 | 17% | 86% | 57%
Week 4 | 25% | 89% | 73%
Week 8 | 36% | 92% | 80%

BOXED WARNING

Figure 1

BOXED WARNING

Figure 2

In two U.S., multicenter double-blind, ranitidine-controlled studies of 925 total patients with frequent GERD symptoms, but no esophageal erosions by endoscopy, lansoprazole 15 mg was superior to ranitidine 150 mg (twice daily) in decreasing the frequency and severity of day and night heartburn associated with GERD for the 8-week treatment period. No significant additional benefit from lansoprazole 30 mg once daily was observed [see Indications and Usage (1.7)].

Erosive Esophagitis

In a U.S. multicenter, double-blind, placebo-controlled study of 269 patients entering with an endoscopic diagnosis of esophagitis with mucosal grading of 2 or more and grades 3 and 4 signifying erosive disease, the percentages of patients with healing are presented in Table 18:

Table 18: Erosive Esophagitis Healing Rates
 | PREVACID
 | 15 mg daily | 30 mg daily | 60 mg daily | Placebo
Week | (N=69) | (N=65) | (N=72) | (N=63)
4 | 67.6% [(p≤0.001) versus placebo.] | 81.3% [(p≤0.05) versus PREVACID 15 mg.] | 80.6% | 32.8%
6 | 87.7% | 95.4% | 94.3% | 52.5%
8 | 90.9% | 95.4% | 94.4% | 52.5%

In this study, all PREVACID groups reported significantly greater relief of heartburn and less day and night abdominal pain along with fewer days of antacid use and fewer antacid tablets taken per day than the placebo group. Although all doses were effective, the earlier healing in the higher two doses suggests 30 mg daily as the recommended dose.

PREVACID was also compared in a U.S. multicenter, double-blind study to a low dose of ranitidine in 242 patients with erosive reflux esophagitis. PREVACID at a dose of 30 mg was significantly more effective than ranitidine 150 mg twice daily as shown below (Table 19).

Table 19: Erosive Esophagitis Healing Rates
Week | PREVACID 30 mg daily (N=115) | Ranitidine 150 mg twice daily (N=127)
2 | 66.7% [(p≤0.001) versus ranitidine.] | 38.7%
4 | 82.5% | 52.0%
6 | 93.0% | 67.8%
8 | 92.1% | 69.9%

In addition, patients treated with PREVACID reported less day and nighttime heartburn and took less antacid tablets for fewer days than patients taking ranitidine 150 mg twice daily.

Although this study demonstrates effectiveness of PREVACID in healing erosive esophagitis, it does not represent an adequate comparison with ranitidine because the recommended ranitidine dose for esophagitis is 150 mg four times daily, twice the dose used in this study.

In the two trials described and in several smaller studies involving patients with moderate to severe erosive esophagitis, PREVACID produced healing rates similar to those shown above.

In a U.S. multicenter, double-blind, active-controlled study, 30 mg of PREVACID was compared with ranitidine 150 mg twice daily in 151 patients with erosive reflux esophagitis that was poorly responsive to a minimum of 12 weeks of treatment with at least one H2-receptor antagonist given at the dose indicated for symptom relief or greater, namely, cimetidine 800 mg/day, ranitidine 300 mg/day, famotidine 40 mg/day or nizatidine 300 mg/day. PREVACID 30 mg was more effective than ranitidine 150 mg twice daily in healing reflux esophagitis, and the percentage of patients with healing were as follows. This study does not constitute a comparison of the effectiveness of histamine H2-receptor antagonists with PREVACID, as all patients had demonstrated unresponsiveness to the histamine H2-receptor antagonist mode of treatment. It does indicate, however, that PREVACID may be useful in patients failing on a histamine H2-receptor antagonist (Table 20) [see Indications and Usage (1.7)].

Table 20: Reflux Esophagitis Healing Rates in Patients Poorly Responsive to Histamine H2-Receptor Antagonist Therapy
Week | PREVACID 30 mg daily (N=100) | Ranitidine 150 mg twice daily (N=51)
4 | 74.7% [(p≤0.001) versus ranitidine.] | 42.6%
8 | 83.7% | 32.0%

Long-Term Maintenance Treatment of Erosive Esophagitis

Two independent, double-blind, multicenter, controlled trials were conducted in patients with endoscopically confirmed healed esophagitis. Patients remained in remission significantly longer and the number of recurrences of erosive esophagitis was significantly less in patients treated with PREVACID than in patients treated with placebo over a 12-month period (Table 21).

Table 21: Endoscopic Remission Rates
 |  |  | Percent in Endoscopic Remission
Trial | Drug | No. of Pts. | 0-3 mo. | 0-6 mo. | 0-12 mo.
#1 | PREVACID 15 mg daily | 59 | 83% [(p≤0.001) versus placebo.] | 81% | 79%
#1 | PREVACID 30 mg daily | 56 | 93% | 93% | 90%
#1 | Placebo | 55 | 31% | 27% | 24%
#2 | PREVACID 15 mg daily | 50 | 74% | 72% | 67%
#2 | PREVACID 30 mg daily | 49 | 75% | 72% | 55%
#2 | Placebo | 47 | 16% | 13% | 13%
%=Life Table Estimate

Regardless of initial grade of erosive esophagitis, PREVACID 15 mg and 30 mg were similar in maintaining remission.

In a U.S., randomized, double-blind, study, PREVACID 15 mg daily (n = 100) was compared with ranitidine 150 mg twice daily (n = 106), at the recommended dosage, in patients with endoscopically-proven healed erosive esophagitis over a 12-month period. Treatment with PREVACID resulted in patients remaining healed (Grade 0 lesions) of erosive esophagitis for significantly longer periods of time than those treated with ranitidine (p<0.001). In addition, PREVACID was significantly more effective than ranitidine in providing complete relief of both daytime and nighttime heartburn. Patients treated with PREVACID remained asymptomatic for a significantly longer period of time than patients treated with ranitidine [see Indications and Usage (1.8)].

Pathological Hypersecretory Conditions Including Zollinger-Ellison Syndrome

In open studies of 57 patients with pathological hypersecretory conditions, such as Zollinger-Ellison syndrome (ZES) with or without multiple endocrine adenomas, PREVACID significantly inhibited gastric acid secretion and controlled associated symptoms of diarrhea, anorexia and pain. Doses ranging from 15 mg every other day to 180 mg per day maintained basal acid secretion below 10 mEq/hr in patients without prior gastric surgery and below 5 mEq/hr in patients with prior gastric surgery.

Initial doses were titrated to the individual patient need, and adjustments were necessary with time in some patients [see Dosage and Administration (2.1)]. PREVACID was well tolerated at these high dose levels for prolonged periods (greater than four years in some patients). In most ZES patients, serum gastrin levels were not modified by PREVACID. However, in some patients, serum gastrin increased to levels greater than those present prior to initiation of lansoprazole therapy [see Indications and Usage (1.9)].

15 REFERENCES

1. National Committee for Clinical Laboratory Standards. Summary Minutes, Subcommittee on Antimicrobial Susceptibility Testing, Tampa, FL, January 11-13, 1998.

16 HOW SUPPLIED/STORAGE AND HANDLING

PREVACID Delayed-Release Capsules 30 mg are opaque, hard gelatin, colored pink and black with "TAP" and "PREVACID 30" imprinted on the capsules. They are available as follows:

NDC 21695-106-15 | Bottles of 15: 30-mg capsules

STORAGE AND HANDLING

Store at 25°C (77°F); excursions permitted to 15-30°C (59-86°F)[see USP Controlled Room Temperature].

17 PATIENT COUNSELING INFORMATION

Patient should be informed of the following:

Information for Patients

PREVACID is available as a capsule and an orally disintegrating tablet, and is available in 15 mg and 30 mg strengths. Directions for use specific to the route and available methods of administration for each of these dosage forms is presented below [see Dosage and Administration (2.3)].

- PREVACID should be taken before eating.
- PREVACID products SHOULD NOT BE CRUSHED OR CHEWED.
- Phenylketonurics: Contains Phenylalanine 2.5 mg per 15 mg Tablet and 5.1 mg per 30 mg Tablet.

Administration Options

- 1 PREVACID Delayed-Release Capsules – Oral Administration
  - PREVACID Delayed-Release Capsules should be swallowed whole.
  - Alternatively, for patients who have difficulty swallowing capsules, PREVACID Delayed-Release Capsules can be opened and administered as follows:
    - Open capsule.
    - Sprinkle intact granules on one tablespoon of either applesauce, ENSURE pudding, cottage cheese, yogurt or strained pears.
    - Swallow immediately.
  - PREVACID Delayed-Release Capsules may also be emptied into a small volume of either apple juice, orange juice or tomato juice and administered as follows:
    - Open capsule.
    - Sprinkle intact granules into a small volume of either apple juice, orange juice or tomato juice (60 mL – approximately 2 ounces).
    - Mix briefly.
    - Swallow immediately.
    - To ensure complete delivery of the dose, the glass should be rinsed with two or more volumes of juice and the contents swallowed immediately.

PREVACID Delayed-Release Capsules – Nasogastric Tube (≥16 French) Administration
  - For patients who have a nasogastric tube in place, PREVACID Delayed-Release Capsules can be administered as follows:
    - Open capsule.
    - Mix intact granules into 40 mL of apple juice. DO NOT USE OTHER LIQUIDS.
    - Inject through the nasogastric tube into the stomach.
    - Flush with additional apple juice to clear the tube.

USE IN OTHER FOODS AND LIQUIDS HAS NOT BEEN STUDIED CLINICALLY AND IS THEREFORE NOT RECOMMENDED.

- 2 PREVACID SoluTab Delayed-Release Orally Disintegrating Tablets
  - PREVACID SoluTab should not be broken or cut.
  - PREVACID SoluTab should not be chewed.
    - Place the tablet on the tongue and allow it to disintegrate, with or without water, until the particles can be swallowed.
    - The tablet typically disintegrates in less than 1 minute.
    - Alternatively, for children or other patients who have difficulty swallowing tablets, PREVACID SoluTab can be delivered in two different ways.
      PREVACID SoluTab – Oral Syringe
      For administration via oral syringe, PREVACID SoluTab can be administered as follows: PREVACID SoluTab – Nasogastric Tube (≥8 French) Administration
      For administration via a nasogastric tube, PREVACID SoluTab can be administered as follows:
      - Place a 15 mg tablet in oral syringe and draw up 4 mL of water, or place a 30 mg tablet in oral syringe and draw up 10 mL of water.
      - Shake gently to allow for a quick dispersal.
      - After the tablet has dispersed, administer the contents within 15 minutes.
      - Refill the syringe with approximately 2 mL (5 mL for the 30 mg tablet) of water, shake gently, and administer any remaining contents.

FDA-Approved Patient Labeling

Patient Information

PREVACID (prev-ǎ-sid)
(lansoprazole)
Delayed-Release Capsules
and
PREVACID SoluTab (prev-ǎ-sid sol-ū-tab)
(lansoprazole)
Delayed-Release Orally Disintegrating Tablets

Read the information that comes with PREVACID before you start taking it and each time you get a refill. There may be new information. This information does not take the place of talking with your doctor about your medical condition or your treatment.

What is PREVACID?

PREVACID is a prescription medicine called a proton pump inhibitor (PPI). PREVACID reduces the amount of acid in your stomach.

PREVACID is used in adults:

- for 4 weeks to heal ulcers in the first part of the small bowel (duodenal ulcers).
- for up to 12 months to stop healed duodenal ulcers from coming back.
- for up to 8 weeks to heal stomach ulcers.
- for up to 8 weeks to heal stomach ulcers in some people taking pain medicines called non-steroidal anti-inflammatory drugs (NSAIDs).
- for reducing the risk of stomach ulcers in some people taking NSAIDs.
- for reducing the risk of stomach infections (Helicobacter pylori), along with antibiotics amoxicillin and clarithromycin.
- for up to 8 weeks for the relief of heartburn and other symptoms of gastroesophageal reflux disease (GERD).
  GERD happens when acid from your stomach enters the tube (esophagus) that connects your mouth to your stomach. This may cause a burning feeling in your chest or throat, sour taste or burping. In some cases, acid can damage the lining of your esophagus. This damage is called erosive esophagitis.
- for 8 weeks to heal the acid-related damage to the lining of the esophagus (called erosive esophagitis) and to relieve symptoms, such as heartburn pain, If needed, your doctor may prescribe an additional 8 weeks of PREVACID.
- to stop erosive esophagitis from coming back (studies lasted 12 months).
- for the long-term treatment of conditions where your stomach makes too much acid. This includes a condition called Zollinger-Ellison syndrome.

PREVACID is used in children and adolescents (ages 1-17):

- for up to 12 weeks to treat GERD and erosive esophagitis, in children 1 to 11 years old.
- for up to 8 weeks to treat GERD and erosive esophagitis, in adolescents 12 to17 years old.

PREVACID is not recommended for children under the age of 1 year.

PREVACID may help your acid-related symptoms, but you could still have serious stomach problems. Talk with your doctor.

Who should not take PREVACID?

Do not take PREVACID if you are allergic to PREVACID or any of its ingredients. See the end of this leaflet for a complete list of ingredients in PREVACID.

What should I tell my doctor before taking PREVACID?

Before you take PREVACID, tell your doctor if you:

- have liver problems
- have phenylketonuria. PREVACID SoluTab contains aspartame.
- have any other medical conditions
- are pregnant or plan to become pregnant. It is not known if PREVACID will harm your unborn baby. Talk to your doctor if you are pregnant or plan to become pregnant.
- are breast-feeding or planning to breast-feed. You and your doctor should decide if you will take PREVACID or breast-feed. You should not do both without first talking with your doctor.

Tell your doctor about all the medicines you take, including prescription and non-prescription medicines, vitamins, and herbal supplements. PREVACID may affect how other medicines work, and other medicines may affect how PREVACID works. Especially tell your doctor if you take:

- ampicillin sodium (Unasyn) or ampicillin trihydrate (Principen)
- atazanavir (Reyataz)
- digoxin (Lanoxicaps, Lanoxin)
- a product that contains iron
- ketoconazole (Nizoral)
- warfarin (Coumadin, Jantoven)
- tacrolimus (Prograf)
- theophylline (Theo-24, Theolair)

Ask your doctor or pharmacist if you are not sure if your medicine is listed above.

How should I take PREVACID?

- Take PREVACID exactly as prescribed by your doctor.
- Do not change your dose or stop taking PREVACID without talking to your doctor first.
- You should take PREVACID before eating.
- PREVACID capsules can be swallowed whole, do not crush or chew them. They can also be opened and sprinkled into approximately ¼ cup apple, tomato or orange juice, or on 1 tablespoon applesauce, Ensure® pudding, cottage cheese, yogurt or strained pears only. See "Patient Instructions for Use" at the end of this leaflet for instructions on how to take PREVACID capsules with these foods, and how to mix and give PREVACID capsules through a nasogastric tube.
- PREVACID SoluTab is a tablet that melts in your mouth with or without water. Do not break, cut or chew the tablets. See "Patient Instructions for Use" at the end of this leaflet for instructions on how to mix and give PREVACID SoluTab tablets through a syringe and nasogastric tube.
- If you miss a dose, take it as soon as you remember. If it is almost time for your next dose, skip the missed dose. Just take the next dose at your regular time. Do not take 2 doses at the same time. If you are not sure about dosing, call your doctor.
- If you take too much PREVACID, call your doctor right away.

What are the possible side effects of PREVACID?

Serious allergic reactions. Tell your doctor if you get any of the following symptoms with PREVACID.

- rash
- face swelling
- throat tightness
- difficulty breathing

Your doctor may stop PREVACID if these symptoms happen.

The most common side effects of PREVACID in adults and children include:

- diarrhea
- stomach pain
- nausea
- constipation
- headache
- dizziness

People who are taking multiple daily doses of proton pump inhibitor medicines for a long period of time may have an increased risk of fractures of the hip, wrist or spine.

Tell your doctor if you have any side effect that bothers you or that does not go away. These are not all the possible side effects of PREVACID. For more information, ask your doctor or pharmacist. Call your doctor for medical advice about side effects. You may report side effects to the FDA at 1-800-FDA-1088.

How should I store PREVACID?

- Store PREVACID at room temperature between 59° to 86°F (15° to 30°C).

Keep PREVACID and all medicines out of the reach of children.

General information about PREVACID

Medicines are sometimes prescribed for conditions other than those listed in a Patient Information Leaflet. Do not use PREVACID for conditions for which it was not prescribed. Do not give PREVACID to other people, even if they have the same symptoms you have. It may harm them.

This Patient Information Leaflet provides a summary of the most important information about PREVACID. For more information, ask your doctor. You can ask your doctor or pharmacist for information that is written for healthcare professionals.

For more information, call 1-877-825-3327.

Patient Instructions for Use

PREVACID Delayed-Release Capsules

- Swallow PREVACID Delayed-Release Capsules whole. Do not crush or chew them.
- If you have trouble swallowing a whole capsule, you can open the capsule and take it with the foods or juices listed below.
  For taking PREVACID Delayed-Release Capsules with applesauce, ENSURE pudding, cottage cheese, yogurt or strained pears:
  For taking PREVACID Delayed-Release Capsules with apple juice, orange juice or tomato juice:
  For giving PREVACID Delayed-Release Capsules through a nasogastric tube (NG tube) ≥16 French, as prescribed by your doctor:
  - Open the capsule.
  - Sprinkle the granules on one tablespoon of either applesauce, ENSURE pudding, cottage cheese, yogurt or strained pears.
  - Swallow right away.

USE IN OTHER FOODS AND LIQUIDS IS NOT RECOMMENDED.

PREVACID SoluTab Delayed-Release Orally Disintegrating Tablets

- Do not chew, crush, cut or break tablets.
  - Put the tablet on the tongue and let it dissolve, with or without water. Swallow after the tablet dissolves.
  - The tablet typically dissolves in less than 1 minute.

- Children or other patients who have trouble swallowing tablets can be given PREVACID SoluTab with an oral syringe or through a nasogastric tube (NG tube) ≥8 French, as prescribed by your doctor.
  For giving PREVACID SoluTab Delayed-Release Orally Disintegrating Tablets with an oral syringe:
  For giving PREVACID SoluTab Delayed-Release Orally Disintegrating Tablets through a nasogastric tube (NG tube) ≥8 French, as prescribed by your doctor:
  - Put a 15 mg tablet in an oral syringe and add 4 mL of water, or put a 30 mg tablet in an oral syringe and add 10 mL of water.
  - Shake the syringe gently to let the tablet dissolve quickly.
  - After the tablet has dissolved, give the medicine within 15 minutes.
  - To make sure that the entire dose is taken, refill the syringe with about 2 mL (5 mL for the 30 mg tablet) of water, shake gently, and give the water in the syringe.

What is in PREVACID?

Active ingredient: lansoprazole.

Inactive ingredients in PREVACID Delayed-Release Capsules:

Sugar sphere, sucrose, methacrylic acid copolymer, low substituted hydroxypropyl cellulose, starch, magnesium carbonate, talc, polyethylene glycol, titanium dioxide, polysorbate 80, hydroxypropyl cellulose, colloidal silicon dioxide, D&C Red No. 28, FD&C Blue No. 1, FD&C Green No. 3 [PREVACID 15-mg capsules only.] , and FD&C Red No. 40.

Inactive ingredients in PREVACID SoluTab Delayed-Release Orally Disintegrating Tablets:

Mannitol, methacrylic acid, hydroxypropyl cellulose, lactose monohydrate-microcrystalline cellulose sphere, triethyl citrate, crospovidone, polyacrylate, magnesium carbonate, aspartame [Phenylketonurics: Contains Phenylalanine 2.5 mg per 15 mg Tablet and 5.1 mg per 30 mg Tablet] , glyceryl monostearate, hypromellose, magnesium stearate, citric acid, titanium dioxide, talc, artificial strawberry flavor, polyethylene glycol, polysorbate 80 and ferric oxide.

Distributed by
Takeda Pharmaceuticals America, Inc.
Deerfield, IL 60015

PREVACID is a trademark registered in the U.S. Patent and Trademark office and SoluTab is a trademark of Takeda Pharmaceuticals North America, Inc. and used under license by Takeda Pharmaceuticals America, Inc.

All other trademark names are the property of their respective owners.

©1995-2010 Takeda Pharmaceuticals America, Inc.

PRV012 R36
August 2010

Repackaged by:

Rebel Distributors Corp

Thousand Oaks, CA 91320